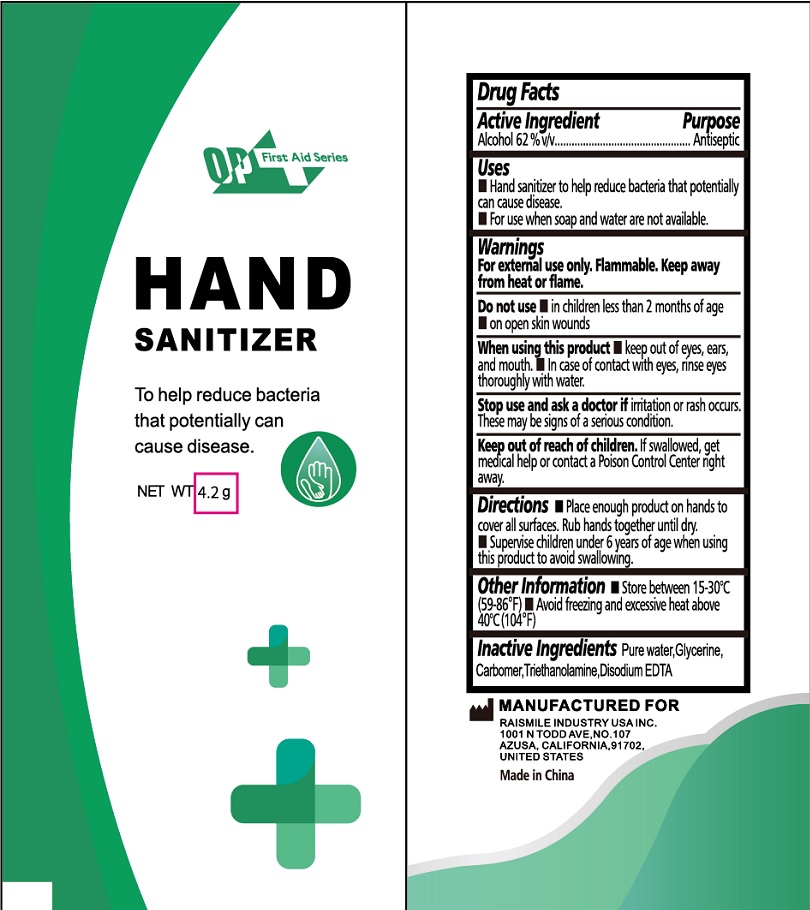 DRUG LABEL: Hand Sanitizer
NDC: 71734-348 | Form: LIQUID
Manufacturer: JIANGMEN SHUIZIRUN SANITARY ARTICLES CO., LTD.
Category: otc | Type: HUMAN OTC DRUG LABEL
Date: 20240531

ACTIVE INGREDIENTS: ALCOHOL 62 g/100 g
INACTIVE INGREDIENTS: GLYCERIN; WATER; TROLAMINE; EDETATE DISODIUM

Drug Fact

Active Ingredient

Alcohol 62%

Purpose

Antiseptic

Uses

Hand sanitizer to help reduce bacterial that potentially can cause disease.

For use when soap and water are not available

Warnings

For external use only. Flammable, keep away from heat or flame.

Do not use in children less than 2 months of age on open skin wounds.

When using this product keep out of eyes ,ears , and mouth. In case of contact with eyes ,rinse eyes thoroughly with water.

Stop use and ask a doctor if iritation or rash occurs. These may be signs of a serious confition.

Keep out of reach of children.

If swallowed get medical help or contact a Posion Control Center immediately.

Directions

Place enough product on hands to cover all surfaces.Rub hands together until dry.

Supervise children under 6 years of age when using this product to avoid swallowing.

Inactive Ingredients

Pure water, Glycerine, Carbomer, Triethanolamine, Disodium EDTA